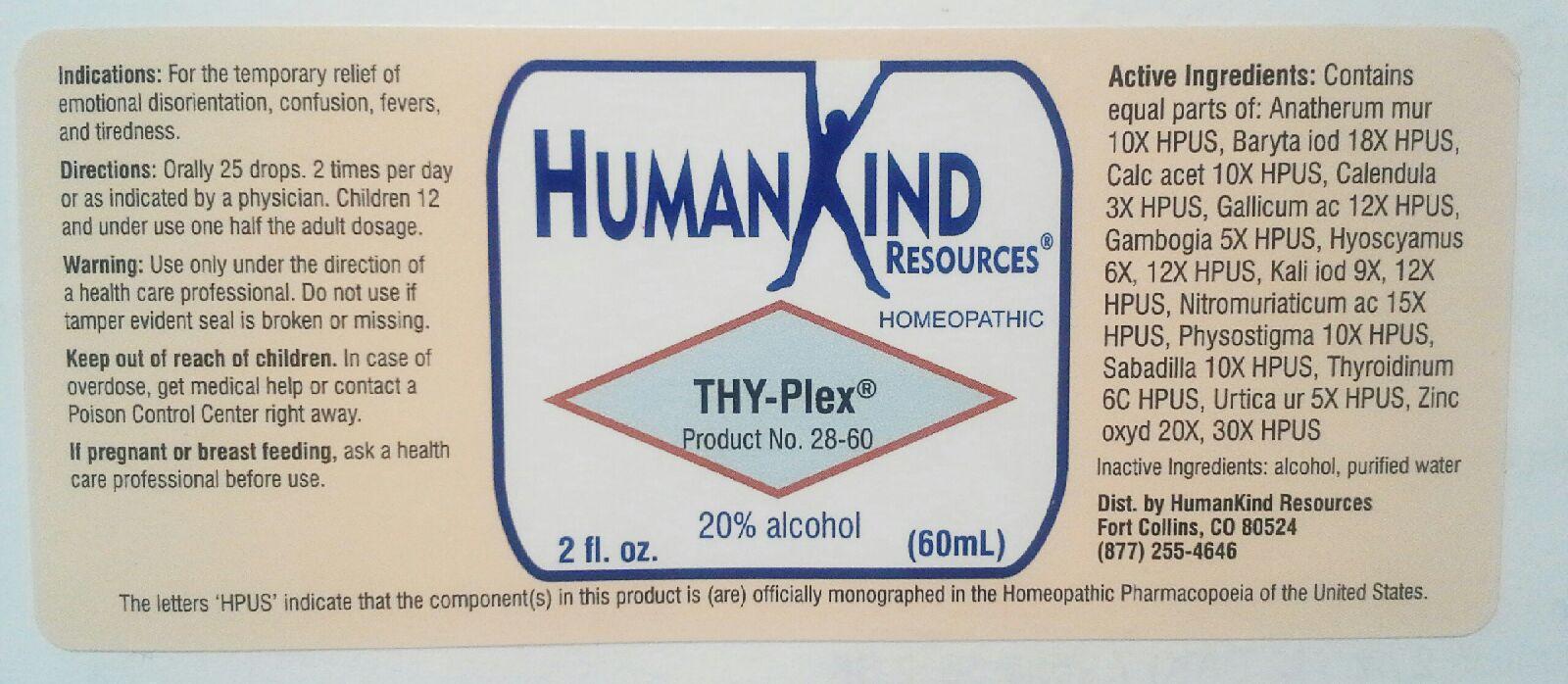 DRUG LABEL: THY-Plex
NDC: 64616-106 | Form: LIQUID
Manufacturer: Vitality Works, Inc.
Category: homeopathic | Type: HUMAN OTC DRUG LABEL
Date: 20251217

ACTIVE INGREDIENTS: CHRYSOPOGON ZIZANIOIDES ROOT 10 [hp_X]/1 mL; BARIUM IODIDE 18 [hp_X]/1 mL; CALCIUM ACETATE 10 [hp_X]/1 mL; CALENDULA OFFICINALIS FLOWERING TOP 3 [hp_X]/1 mL; GALLIC ACID MONOHYDRATE 12 [hp_X]/1 mL; GAMBOGE 5 [hp_X]/1 mL; HYOSCYAMUS NIGER 12 [hp_X]/1 mL; POTASSIUM IODIDE 12 [hp_X]/1 mL; AQUA REGIA 15 [hp_X]/1 mL; PHYSOSTIGMA VENENOSUM SEED 10 [hp_X]/1 mL; SCHOENOCAULON OFFICINALE SEED 10 [hp_X]/1 mL; THYROID, UNSPECIFIED 6 [hp_C]/1 mL; URTICA URENS 5 [hp_X]/1 mL; ZINC OXIDE 30 [hp_X]/1 mL
INACTIVE INGREDIENTS: ALCOHOL; WATER

THY-Plex

THY-Plex

Anatherum Muricatum 10X Kali Iodatum 9X, 12X

Baryta Iodata 18X Nitromuriaticum Acidum 15X

Calcarea Acetica 10X Physostigma Venenosum 10X

Calendula Officinalis 3X Sabadilla 10X

Gallicum Acidum 12X Thyroidinum 6C

Gambogia 5x Urtica Urens 5X

Hyoscyamus Niger 6X, 12X Zincum Oxydatum 20X, 30X

THY-Plex

Alcohol, Purified Water

THY-Plex

Use only under the direction of a health care professional. Do not use if tamper evident seal is broken or missing.

THY-Plex

Keep out of reach of children. In case of overdose, get medical help or contract a Poison Control Center right away.

THY-Plex

For the temporary relief of emotional disorientation, confusion, fevers, and tiredness

THY-Plex

Orally 25 drops, 2 times per day or as indicated by a physician. Children 12 and under, use one half the adult doseage.

THY-Plex

Aids in temporary Thyroid Gland support.